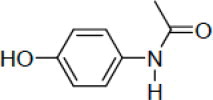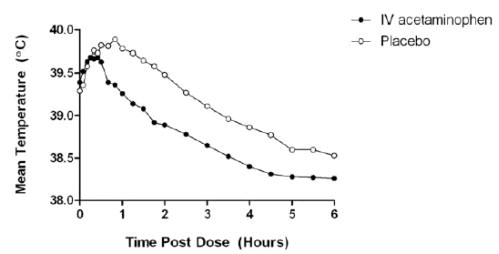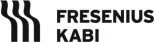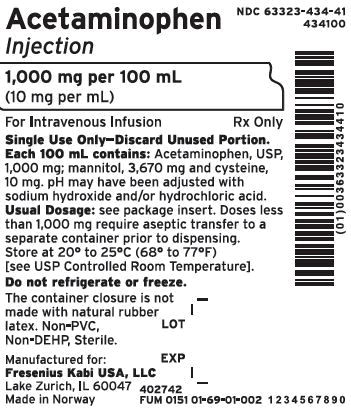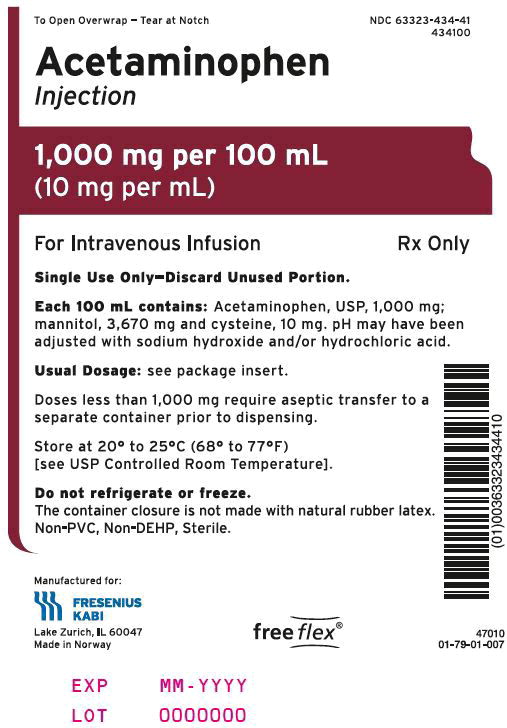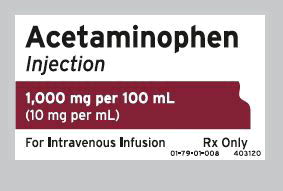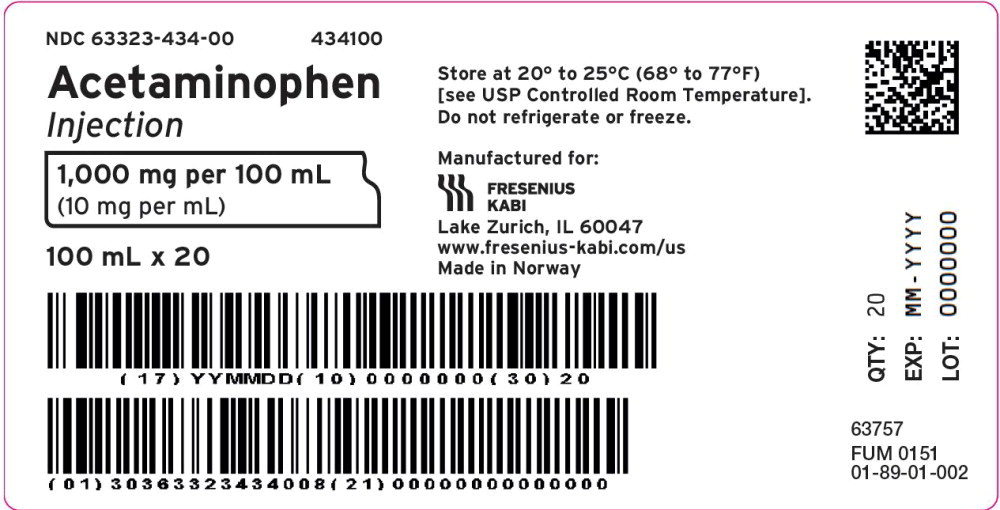 DRUG LABEL: Acetaminophen
NDC: 63323-434 | Form: INJECTION
Manufacturer: Fresenius Kabi USA, LLC
Category: prescription | Type: HUMAN PRESCRIPTION DRUG LABEL
Date: 20240424

ACTIVE INGREDIENTS: ACETAMINOPHEN 10 mg/1 mL
INACTIVE INGREDIENTS: MANNITOL; CYSTEINE HYDROCHLORIDE; SODIUM HYDROXIDE; HYDROCHLORIC ACID

HIGHLIGHTS OF PRESCRIBING INFORMATION

These highlights do not include all the information needed to use ACETAMINOPHEN INJECTION safely and effectively. See full prescribing information for ACETAMINOPHEN INJECTION.
ACETAMINOPHEN injection, for intravenous use
Initial U.S. Approval: 1951

WARNING: Risk of Medication Errors and Hepatotoxicity

See full prescribing information for complete boxed warning

Take care when prescribing, preparing, and administering Acetaminophen Injection to avoid dosing errors which could result in accidental overdose and death.

Acetaminophen Injection contains acetaminophen. Acetaminophen has been associated with cases of acute liver failure, at times resulting in liver transplant and death. Most of the cases of liver injury are associated with the use of acetaminophen at doses that exceed the recommended maximum daily limits, and often involve more than one acetaminophen-containing product. (5.1)

1 INDICATIONS AND USAGE

Acetaminophen Injection is indicated for the

- Management of mild to moderate pain in adult and pediatric patients 2 years and older (1)
- Management of moderate to severe pain with adjunctive opioid analgesics in adult and pediatric patients 2 years and older (1)
- Reduction of fever in adult and pediatric patients 2 years and older (1)

2 DOSAGE AND ADMINISTRATION

- Acetaminophen Injection may be given as a single or repeated dose. (2.1)
- Acetaminophen Injection should be administered only as a 15-minute intravenous infusion. (2.4)

Adults and Adolescents Weighing 50 kg and Over:

- 1,000 mg every 6 hours or 650 mg every 4 hours to a maximum of 4,000 mg per day. Minimum dosing interval of 4 hours. (2.2)

Adults and Adolescents Weighing Under 50 kg:

- 15 mg/kg every 6 hours or 12.5 mg/kg every 4 hours to a maximum of 75 mg/kg per day. Minimum dosing interval of 4 hours. (2.2)

Children:

- Children 2 to 12 years of age: 15 mg/kg every 6 hours or 12.5 mg/kg every 4 hours to a maximum of 75 mg/kg per day. Minimum dosing interval of 4 hours. (2.3)

3 DOSAGE FORMS AND STRENGTHS

- Injection for intravenous infusion.
- Each 100 mL single-dose flexible bag contains 1,000 mg acetaminophen (10 mg/mL). (3)

4 CONTRAINDICATIONS

Acetaminophen is contraindicated:

- In patients with known hypersensitivity to acetaminophen or to any of the excipients in the IV formulation. (4)
- In patients with severe hepatic impairment or severe active liver disease. (4)

5 WARNINGS AND PRECAUTIONS

- Administration of acetaminophen in doses higher than recommended (by all routes of administration and from all acetaminophen-containing products including combination products) may result in hepatic injury, including the risk of liver failure and death. (5.1)
- Use caution when administering acetaminophen in patients with the following conditions: hepatic impairment or active hepatic disease, in cases of alcoholism, chronic malnutrition, severe hypovolemia, or severe renal impairment (creatinine clearance ≤ 30 mL/min). (5.1)
- Discontinue acetaminophen immediately at the first appearance of skin rash and if symptoms associated with allergy or hypersensitivity occur. Do not use in patients with acetaminophen allergy. (5.2, 5.4)
- Take care when prescribing, preparing, and administering acetaminophen injection to avoid dosing errors which could result in accidental overdose and death. (5.3)

6 ADVERSE REACTIONS

The most common adverse reactions in patients treated with acetaminophen were nausea, vomiting, headache, and insomnia in adult patients; nausea, vomiting, constipation, pruritus, agitation, and atelectasis in pediatric patients. (6.1)

To report SUSPECTED ADVERSE REACTIONS, contact Fresenius Kabi USA, LLC at 1-800-551- 7176 or FDA at 1-800-FDA-1088 or www.fda.gov/medwatch.

7 DRUG INTERACTIONS

- Substances that induce or regulate hepatic cytochrome enzyme CYP2E1 may alter the metabolism of acetaminophen and increase its hepatotoxic potential. (7.1)
- Chronic oral acetaminophen use at a dose of 4,000 mg/day has been shown to cause an increase in international normalized ratio (INR) in some patients who have been stabilized on sodium warfarin as an anticoagulant. (7.2)

8 USE IN SPECIFIC POPULATIONS

- Pediatric Use: The effectiveness of acetaminophen for the treatment of acute pain in pediatric patients younger than 2 years of age has not been established. The safety and effectiveness of acetaminophen in pediatric patients older than 2 years of age is supported by evidence from adequate and well-controlled studies in adults with additional safety and pharmacokinetic data for this age group. (8.4)
- Geriatric Use: No overall differences in safety or effectiveness were observed between geriatric and younger subjects. (8.5)
- Hepatic Impairment: Acetaminophen is contraindicated in patients with severe hepatic impairment or severe active liver disease and should be used with caution in patients with hepatic impairment or active liver disease. (4, 5.1, 8.6)
- Renal Impairment: In cases of severe renal impairment, longer dosing intervals and a reduced total daily dose of acetaminophen may be warranted. (5.1, 8.7)

FULL PRESCRIBING INFORMATION

WARNING: Risk of Medication Errors and Hepatotoxicity

Take care when prescribing, preparing, and administering Acetaminophen Injection to avoid dosing errors which could result in accidental overdose and death. In particular, be careful to ensure that:

- the dose in milligrams (mg) and milliliters (mL) is not confused;
- the dosing is based on weight for patients under 50 kg;
- infusion pumps are properly programmed; and
- the total daily dose of acetaminophen from all sources does not exceed maximum daily limits.

Acetaminophen Injection contains acetaminophen. Acetaminophen has been associated with cases of acute liver failure, at times resulting in liver transplant and death. Most of the cases of liver injury are associated with the use of acetaminophen at doses that exceed the maximum daily limits, and often involve more than one acetaminophen-containing product [see Warnings and Precautions (5.1)].

1 INDICATIONS AND USAGE

Acetaminophen Injection is indicated for

- the management of mild to moderate pain in adult and pediatric patients 2 years and older
- the management of moderate to severe pain with adjunctive opioid analgesics in adult and pediatric patients 2 years and older
- the reduction of fever in adult and pediatric patients 2 years and older.

2 DOSAGE AND ADMINISTRATION

2.1 General Dosing Information

Acetaminophen Injection, for intravenous use, may be given as a single or repeated dose for the treatment of acute pain or fever. No dose adjustment is required when converting between oral acetaminophen and acetaminophen injection dosing in adults and adolescents who weigh 50 kg and above. Calculated maximum daily dose of acetaminophen is based on all routes of administration (i.e., intravenous, oral, and rectal) and all products containing acetaminophen. Exceeding the maximum mg/kg daily dose of acetaminophen as described in Tables 1 and 2 may result in hepatic injury, including the risk of liver failure and death.

To avoid the risk of overdose, ensure that the total amount of acetaminophen from all routes and from all sources does not exceed the maximum recommended dose.

2.2 Recommended Dosage: Adults and Adolescents

Adults and adolescents weighing 50 kg and over: the recommended dosage of acetaminophen injection is 1,000 mg every 6 hours or 650 mg every 4 hours, with a maximum single dose of acetaminophen injection of 1,000 mg, a minimum dosing interval of 4 hours, and a maximum daily dose of acetaminophen of 4,000 mg per day (includes all routes of administration and all acetaminophen-containing products including combination products).

Adults and adolescents weighing under 50 kg: the recommended dosage of acetaminophen injection is 15 mg/kg every 6 hours or 12.5 mg/kg every 4 hours, with a maximum single dose of acetaminophen injection of 15 mg/kg, a minimum dosing interval of 4 hours, and a maximum daily dose of acetaminophen of 75 mg/kg per day (includes all routes of administration and all acetaminophen-containing products including combination products).

Table 1. Dosing for Adults and Adolescents
Age group | Dose given every 4 hours | Dose given every 6 hours | Maximum single dose | Maximum total daily dose of acetaminophen (by all routes)
Adults and adolescents (13 years and older) weighing ≥ 50 kg | 650 mg | 1,000 mg | 1,000 mg | 4,000 mg in 24 hours
Adults and adolescents (13 years and older) weighing < 50 kg | 12.5 mg/kg | 15 mg/kg | 15 mg/kg (up to 750 mg) | 75 mg/kg in 24 hours (up to 3,750 mg)

2.3 Recommended Dosage: Children

Children 2 to 12 years of age: the recommended dosage of acetaminophen injection is 15 mg/kg every 6 hours or 12.5 mg/kg every 4 hours, with a maximum single dose of acetaminophen injection of 15 mg/kg, a minimum dosing interval of 4 hours, and a maximum daily dose of acetaminophen of 75 mg/kg per day.

Table 2. Dosing for Children
Age group | Dose given every 4 hours | Dose given every 6 hours | Maximum single dose | Maximum total daily dose of acetaminophen (by all routes)
Children 2 to 12 years of age | 12.5 mg/kg | 15 mg/kg | 15 mg/kg (up to 750 mg) | 75 mg/kg in 24 hours (up to 3,750 mg)

2.4 Instructions for Intravenous Administration

For adult and adolescent patients weighing ≥ 50 kg requiring 1,000 mg doses of acetaminophen injection, administer the dose by inserting an intravenous set through the administration spike port of the 100 mL bag. Acetaminophen Injection may be administered without further dilution. Examine the flexible bag contents before dose preparation or administering. DO NOT USE if particulate matter or discoloration is observed. Administer the contents of the flexible bag intravenously over 15 minutes. Use aseptic technique when preparing acetaminophen injection for intravenous infusion. Do not add other medications to the acetaminophen injection flexible bag.

For doses less than 1,000 mg, the appropriate dose must be withdrawn from the acetaminophen injection flexible bag and placed into a separate container prior to administration. Using aseptic technique, withdraw the appropriate dose (650 mg or weight-based) from an intact sealed acetaminophen injection flexible bag using a spike adaptor with an external spike diameter between 5.5 mm to 5.7 mm and 27 mm to 29 mm in length in accordance with ISO 8536-4. Place the measured dose in a separate empty, sterile container (e.g., glass bottle, plastic intravenous container, or syringe) for intravenous infusion to avoid the inadvertent delivery and administration of the total volume of the commercially available container. The entire 100 mL flexible bag of acetaminophen injection is not intended for use in patients weighing less than 50 kg.

Acetaminophen Injection is supplied in a single-dose flexible bag and the unused portion must be discarded.

Place small volume pediatric doses up to 60 mL in volume in a syringe and administer over 15 minutes using a syringe pump.

Monitor the end of the infusion in order to prevent the possibility of an air embolism, especially in cases where the Acetaminophen Injection infusion is the primary infusion.

Once the seal of the flexible bag has been penetrated, or the contents transferred to another container, administer the dose of acetaminophen injection within 6 hours.

For bags, refrain from applying excessive pressure causing distortion to the bag, such as wringing or twisting, since such handling could result in breakage of the bag.

Do not add other medications to the acetaminophen injection solution. Diazepam and chlorpromazine hydrochloride are physically incompatible with acetaminophen injection, therefore do not administer simultaneously.

3 DOSAGE FORMS AND STRENGTHS

Acetaminophen Injection is a sterile, clear, colorless, non-pyrogenic, preservative free, isotonic formulation of acetaminophen intended for intravenous infusion. Each 100 mL single-dose flexible bag contains 1,000 mg acetaminophen (10 mg/mL).

4 CONTRAINDICATIONS

Acetaminophen is contraindicated:

- in patients with known hypersensitivity to acetaminophen or to any of the excipients in the intravenous formulation.
- in patients with severe hepatic impairment or severe active liver disease [see Warnings and Precautions (5.1)].

5 WARNINGS AND PRECAUTIONS

5.1 Hepatic Injury

Administration of acetaminophen in doses higher than recommended may result in hepatic injury, including the risk of liver failure and death [see Overdosage (10)]. Do not exceed the maximum recommended daily dose of acetaminophen [see Dosage and Administration (2)]. The maximum recommended daily dose of acetaminophen includes all routes of administration and all acetaminophen-containing products administered, including combination products.

Use caution when administering acetaminophen in patients with the following conditions: hepatic impairment or active hepatic disease, alcoholism, chronic malnutrition, severe hypovolemia (e.g., due to dehydration or blood loss), or severe renal impairment (creatinine clearance ≤ 30 mL/min) [see Use in Specific Populations (8.6, 8.7)].

5.2 Serious Skin Reactions

Rarely, acetaminophen may cause serious skin reactions such as acute generalized exanthematous pustulosis (AGEP), Stevens-Johnson Syndrome (SJS), and toxic epidermal necrolysis (TEN), which can be fatal. Patients should be informed about the signs of serious skin reactions, and use of the drug should be discontinued at the first appearance of skin rash or any other sign of hypersensitivity.

5.3 Risk of Medication Errors

Take care when prescribing, preparing, and administering acetaminophen injection in order to avoid dosing errors which could result in accidental overdose and death. In particular, be careful to ensure that:

- the dose in milligrams (mg) and milliliters (mL) is not confused;
- the dosing is based on weight for patients under 50 kg;
- infusion pumps are properly programmed; and
- the total daily dose of acetaminophen from all sources does not exceed maximum daily limits [see Dosage and Administration (2)].

5.4 Allergy and Hypersensitivity

There have been post-marketing reports of hypersensitivity and anaphylaxis associated with the use of acetaminophen. Clinical signs included swelling of the face, mouth, and throat, respiratory distress, urticaria, rash, and pruritus. There were infrequent reports of life-threatening anaphylaxis requiring emergent medical attention. Discontinue acetaminophen immediately if symptoms associated with allergy or hypersensitivity occur. Do not use acetaminophen in patients with acetaminophen allergy.

6 ADVERSE REACTIONS

The following serious adverse reactions are discussed elsewhere in the labeling:

- Hepatic Injury [see Warnings and Precautions (5.1)]
- Serious Skin Reactions [see Warnings and Precautions (5.2)]
- Allergy and Hypersensitivity [see Warnings and Precautions (5.4)]

6.1 Clinical Trial Experience

Because clinical trials are conducted under widely varying conditions, adverse reaction rates observed cannot be directly compared to rates in other clinical trials and may not reflect the rates observed in practice.

Adult Population

A total of 1,020 adult patients have received acetaminophen in clinical trials, including 37.3% (n=380) who received 5 or more doses, and 17% (n=173) who received more than 10 doses. Most patients were treated with acetaminophen 1,000 mg every 6 hours. A total of 13.1% (n=134) received acetaminophen 650 mg every 4 hours.

All adverse reactions that occurred in adult patients treated with either acetaminophen or placebo in repeated dose, placebo-controlled clinical trials at an incidence ≥ 3% and at a greater frequency than placebo are listed in Table 3. The most common adverse events in adult patients treated with acetaminophen (incidence ≥ 5% and greater than placebo) were nausea, vomiting, headache, and insomnia.

Table 3. Treatment-Emergent Adverse Reactions Occurring in ≥ 3% of Acetaminophen- treated Adult Patients and at a Greater Frequency than Placebo in Placebo-Controlled, Repeated Dose Studies
System Organ Class - Preferred Term | Acetaminophen (N=402) n (%) | Placebo (N=379) n (%)
Gastrointestinal Disorders Nausea Vomiting | 138 (34) 62 (15) | 119 (31) 42 (11)
General Disorders and Administration Site Conditions Pyrexia* | 22 (5) | 52 (14)
Nervous System Disorders Headache | 39 (10) | 33 (9)
Psychiatric Disorders Insomnia | 30 (7) | 21 (5)
* Pyrexia adverse reaction frequency data is included in order to alert healthcare practitioners that the antipyretic effects of acetaminophen may mask fever.

Other Adverse Reactions Observed During Clinical Studies of Acetaminophen in Adults

The following additional treatment-emergent adverse reactions were reported by adult subjects treated with acetaminophen in all clinical trials (n=1,020) that occurred with an incidence of at least 1% and at a frequency greater than placebo (n=525).

Blood and lymphatic system disorders: anemia

General disorders and administration site conditions: fatigue, infusion site pain, edema peripheral

Investigations: aspartate aminotransferase increased, breath sounds abnormal

Metabolism and nutrition disorders: hypokalemia

Musculoskeletal and connective tissue disorders: muscle spasms, trismus

Psychiatric disorders: anxiety

Respiratory, thoracic and mediastinal disorders: dyspnea

Vascular disorders: hypertension, hypotension

Pediatric Population

A total of 355 pediatric patients (47 neonates, 64 infants, 171 children, and 73 adolescents) have received acetaminophen in active-controlled (n=250) and open-label clinical trials (n=225), including 59.7% (n=212) who received 5 or more doses and 43.1% (n=153) who received more than 10 doses. Pediatric patients received acetaminophen doses up to 15 mg/kg on an every 4 hours, every 6 hours, or every 8 hours schedule. The maximum exposure was 7.7, 6.4, 6.8, and 7.1 days in neonates, infants, children, and adolescents, respectively.

The most common adverse events (incidence ≥ 5%) in pediatric patients treated with acetaminophen were nausea, vomiting, constipation, pruritus, agitation, and atelectasis.

Other Adverse Reactions Observed During Clinical Studies of Acetaminophen in Pediatrics The following additional treatment-emergent adverse reactions were reported by pediatric subjects treated with acetaminophen (n=355) that occurred with an incidence of at least 1%.

Blood and lymphatic system disorders: anemia

Cardiac disorders: tachycardia

Gastrointestinal disorders: abdominal pain, diarrhea

General disorders and administration site conditions: pyrexia, injection site pain, edema peripheral

Metabolism and nutrition disorders: hypokalemia, hypomagnesemia, hypoalbuminemia, hypophosphatemia, hypervolemia

Musculoskeletal and connective tissue disorders: muscle spasm, pain in extremity

Nervous system disorders: headache

Psychiatric disorders: insomnia

Renal and urinary disorders: oliguria

Respiratory, thoracic and mediastinal disorders: hypoxia, pleural effusion, pulmonary edema, stridor, wheezing

Skin and subcutaneous tissue disorders: periorbital edema, rash

Vascular disorders: hypotension, hypertension

7 DRUG INTERACTIONS

7.1 Effects of Other Substances on Acetaminophen

Substances that induce or regulate hepatic cytochrome enzyme CYP2E1 may alter the metabolism of acetaminophen and increase its hepatotoxic potential. The clinical consequences of these effects have not been established. Effects of ethanol are complex, because excessive alcohol usage can induce hepatic cytochromes, but ethanol also acts as a competitive inhibitor of the metabolism of acetaminophen.

7.2 Anticoagulants

Chronic oral acetaminophen use at a dose of 4,000 mg/day has been shown to cause an increase in international normalized ratio (INR) in some patients who have been stabilized on sodium warfarin as an anticoagulant. As no studies have been performed evaluating the short-term use of acetaminophen in patients on oral anticoagulants, more frequent assessment of INR may be appropriate in such circumstances.

8 USE IN SPECIFIC POPULATIONS

8.1 Pregnancy

Risk Summary

Prolonged experience with acetaminophen in pregnant women over several decades, based on published observational epidemiological studies and case reports, did not identify a drug associated risk of major birth defects, miscarriage, or adverse maternal or fetal outcomes (see Data). Animal reproduction studies have not been conducted with IV acetaminophen. Reproductive and developmental studies in rats and mice from the published literature identified adverse events at clinically relevant doses with acetaminophen. Treatment of pregnant rats with doses of acetaminophen approximately equal to the maximum human daily dose (MHDD) showed evidence of fetotoxicity and increases in bone variations in the fetuses. In another study, necrosis was observed in the liver and kidney of both pregnant rats and fetuses at doses approximately equal to the MHDD. In mice and rats treated with acetaminophen at doses within the clinical dosing range, cumulative adverse effects on reproductive capacity were reported. In mice, a reduction in number of litters of the parental mating pair was observed as well as retarded growth, abnormal sperm in their offspring and reduced birth weight in the next generation. In rats, female fertility was decreased following in utero exposure to acetaminophen (see Data).

The estimated background risk of major birth defects and miscarriages for the indicated population is unknown. All pregnancies have a background risk of birth defect, loss, or other adverse outcomes. In the U.S. general population, the estimated background risk of major birth defects and miscarriage in clinically recognized pregnancies is 2-4% and 15-20%, respectively.

Data

Human Data

The results from a large population-based prospective cohort, including data from 26,424 women with live born singletons who were exposed to oral acetaminophen during the first trimester, indicate no increased risk for congenital malformations, compared to a control group of unexposed children. The rate of congenital malformations (4.3%) was similar to the rate in the general population. A population-based, case-control study from the National Birth Defects Prevention Study showed that 11,610 children with prenatal exposure to acetaminophen during the first trimester had no increased risk of major birth defects compared to 4,500 children in the control group. Other epidemiological data showed similar results. However, these studies cannot definitively establish the absence of any risk because of methodological limitations, including recall bias.

Animal Data

Studies in pregnant rats that received oral acetaminophen during organogenesis at doses up to 0.85 times the maximum human daily dose (MHDD = 4 grams/day, based on a body surface area comparison) showed evidence of fetotoxicity (reduced fetal weight and length) and a dose-related increase in bone variations (reduced ossification and rudimentary rib changes). Offspring had no evidence of external, visceral, or skeletal malformations. When pregnant rats received oral acetaminophen throughout gestation at doses of 1.2 times the MHDD (based on a body surface area comparison), areas of necrosis occurred in both the liver and kidney of pregnant rats and fetuses. These effects did not occur in animals that received oral acetaminophen at doses 0.3 times the MHDD, based on a body surface area comparison.

In a continuous breeding study, pregnant mice received 0.25, 0.5, or 1% acetaminophen via the diet (357, 715, or 1,430 mg/kg/day). These doses are approximately 0.43, 0.87, and 1.7 times the MHDD, respectively, based on a body surface area comparison. A dose related reduction in body weights of fourth and fifth litter offspring of the treated mating pair occurred during lactation and post-weaning at all doses. Animals in the high dose group had a reduced number of litters per mating pair, male offspring with an increased percentage of abnormal sperm, and reduced birth weights in the next generation pups.

8.2 Lactation

Risk Summary

There is no information regarding the presence of acetaminophen in human milk, the effects on the breastfed infant, or the effects on milk production. However, limited published studies report that acetaminophen passes rapidly into human milk with similar levels in the milk and plasma. Average and maximum neonatal doses of 1% and 2%, respectively, of the weight-adjusted maternal dose are reported after a single oral administration of 1 gram APAP. There is one well-documented report of a rash in a breast-fed infant that resolved when the mother stopped acetaminophen use and recurred when she resumed acetaminophen use. The developmental and health benefits of breastfeeding should be considered along with the mother's clinical need for acetaminophen injection and any potential adverse effects on the breastfed infant from acetaminophen injection or from the underlying maternal condition.

8.3 Females and Males of Reproductive Potential

Based on animal data use of acetaminophen may cause reduced fertility in males and females of reproductive potential. It is not known whether these effects on fertility are reversible. Published animal studies reported that oral acetaminophen treatment of male animals at doses that are 1.2 times the MHDD and greater (based on a body surface area comparison) result in decreased testicular weights, reduced spermatogenesis, and reduced fertility. In female animals given the same doses, reduced implantation sites were reported. Additional published animal studies indicate that acetaminophen exposure in utero adversely impacts reproductive capacity of both male and female offspring at clinically relevant exposures [see Nonclinical Toxicology (13.1)].

8.4 Pediatric Use

Treatment of Acute Pain

The safety and effectiveness of acetaminophen for the treatment of acute pain in pediatric patients ages 2 years and older is supported by evidence from adequate and well- controlled studies of acetaminophen in adults and safety and pharmacokinetic data from adult and 355 pediatric patients across all age groups [see Dosage and Administration (2.3) and Pharmacokinetics (12.3)].

The effectiveness of acetaminophen for the treatment of acute pain in pediatric patients younger than 2 years of age has not been established.

Treatment of Fever

The safety and effectiveness of acetaminophen injection for the treatment of fever in pediatric patients is supported by adequate and well-controlled studies of acetaminophen injection in adults and clinical studies in 244 pediatric patients 2 years and older.

8.5 Geriatric Use

Of the total number of subjects in clinical studies of acetaminophen, 15% were age 65 and over, while 5% were age 75 and over. No overall differences in safety or effectiveness were observed between these subjects and younger subjects, and other reported clinical experience has not identified differences in responses between the elderly and younger patients, but greater sensitivity of some older individuals cannot be ruled out.

8.6 Patients with Hepatic Impairment

Acetaminophen is contraindicated in patients with severe hepatic impairment or severe active liver disease and should be used with caution in patients with hepatic impairment or active liver disease [see Warnings and Precautions (5.1) and Clinical Pharmacology (12)]. A reduced total daily dose of acetaminophen may be warranted.

8.7 Patients with Renal Impairment

In cases of severe renal impairment (creatinine clearance ≤ 30 mL/min), longer dosing intervals and a reduced total daily dose of acetaminophen may be warranted.

10 OVERDOSAGE

Signs and Symptoms

In acute acetaminophen overdosage, dose-dependent, potentially fatal hepatic necrosis is the most serious adverse effect. Renal tubular necrosis, hypoglycemic coma, and thrombocytopenia may also occur. Plasma acetaminophen levels > 300 mcg/mL at 4 hours after oral ingestion were associated with hepatic damage in 90% of patients; minimal hepatic damage is anticipated if plasma levels at 4 hours are < 150 mcg/mL or < 37.5 mcg/mL at 12 hours after ingestion. Early symptoms following a potentially hepatotoxic overdose may include: nausea, vomiting, diaphoresis, and general malaise. Clinical and laboratory evidence of hepatic toxicity may not be apparent until 48 to 72 hours post-ingestion.

Treatment

If an acetaminophen overdose is suspected, obtain a serum acetaminophen assay as soon as possible, but no sooner than 4 hours following oral ingestion. Obtain liver function studies initially and repeat at 24-hour intervals. Administer the antidote N-acetylcysteine (NAC) as early as possible. As a guide to treatment of acute ingestion, the acetaminophen level can be plotted against time since oral ingestion on a nomogram (Rumack-Matthew). The lower toxic line on the nomogram is equivalent to 150 mcg/mL at 4 hours and 37.5 mcg/mL at 12 hours. If serum level is above the lower line, administer the entire course of NAC treatment. Withhold NAC therapy if the acetaminophen level is below the lower line.

For additional information, call a poison control center at 1-800-222-1222.

11 DESCRIPTION

Acetaminophen is a non-salicylate antipyretic and non-opioid analgesic agent. Its chemical name is N-acetyl-p-aminophenol. Its structural formula is:

M.W. 151.16

Acetaminophen Injection, for intravenous use, is a sterile, clear, colorless, non-pyrogenic, isotonic formulation of acetaminophen intended for intravenous infusion. Each 100 mL contains 1,000 mg of Acetaminophen, USP; 3,670 mg of mannitol, 10 mg of cysteine, and hydrochloric acid and sodium hydroxide as pH adjusters, in water for injection. Acetaminophen Injection has a pH between 5.0 and 6.3, and an osmolality of approximately 290 mOsm/kg.

12 CLINICAL PHARMACOLOGY

12.1 Mechanism of Action

The precise mechanism of the analgesic and antipyretic properties of acetaminophen is not established but is thought to primarily involve central actions.

12.2 Pharmacodynamics

Acetaminophen has been shown to have analgesic and antipyretic activities in animal and human studies.

Single doses of acetaminophen up to 3,000 mg and repeated doses of 1,000 mg every 6 hours for 48 hours have not been shown to cause a significant effect on platelet aggregation. Acetaminophen does not have any immediate or delayed effects on small-vessel hemostasis. Clinical studies of both healthy subjects and patients with hemophilia showed no significant changes in bleeding time after receiving multiple doses of oral acetaminophen.

12.3 Pharmacokinetics

Distribution

The pharmacokinetics of acetaminophen have been studied in patients and healthy subjects up to 60 years old. The pharmacokinetic profile of acetaminophen has been demonstrated to be dose proportional in adults following administration of single doses of 500, 650, and 1,000 mg.

The maximum concentration (Cmax) occurs at the end of the 15-minute intravenous infusion of acetaminophen. Compared to the same dose of oral acetaminophen, the Cmax following administration of acetaminophen is up to 70% higher, while overall exposure (area under the concentration time curve [AUC]) is very similar.

Pharmacokinetic parameters of acetaminophen (AUC, Cmax, terminal elimination half-life [T1/2], systemic clearance [CL], and volume of distribution at steady state [Vss]) following administration of a single intravenous dose of 15 mg/kg in children and adolescents and 1,000 mg in adults are summarized in Table 4.

Table 4. Acetaminophen Pharmacokinetic Parameters
Subpopulations | Mean (SD)
Subpopulations | AUC 0-6h (μg x h/mL) | Cmax (μg/mL) | T 1/2 (h) | CL (L/h/kg) | Vss (L/kg)
Neonates | 62 (11) | 25 (4) | 7 (2.7) | 0.12 (0.04) | 1.1 (0.2)
Infants | 57 (54) | 29 (24) | 4.2 (2.9) | 0.29 (0.15) | 1.1 (0.3)
Children | 38 (8) | 29 (7) | 3 (1.5) | 0.34 (0.10) | 1.2 (0.3)
Adolescents | 41 (7) | 31 (9) | 2.9 (0.7) | 0.29 (0.08) | 1.1 (0.3)
Adults | 43 (11) | 28 (21) | 2.4 (0.6) | 0.27 (0.08) | 0.8 (0.2)

The pharmacokinetic exposure of acetaminophen observed in children and adolescents is similar to adults, but higher in neonates and infants. Dosing simulations from pharmacokinetic data in infants and neonates suggest that dose reductions of 33% in infants 1 month to < 2 years of age, and 50% in neonates up to 28 days, with a minimum dosing interval of 6 hours, will produce a pharmacokinetic exposure similar to that observed in children age 2 years and older.

At therapeutic levels, binding of acetaminophen to plasma proteins is low (ranging from 10% to 25%). Acetaminophen appears to be widely distributed throughout most body tissues except fat.

Metabolism and Excretion

Acetaminophen is primarily metabolized in the liver by first-order kinetics and involves three principal separate pathways: Conjugation with glucuronide, conjugation with sulfate, and oxidation via the cytochrome P450 enzyme pathway, primarily CYP2E1, to form a reactive intermediate metabolite (N-acetyl-p-benzoquinone imine or NAPQI). With therapeutic doses, NAPQI undergoes rapid conjugation with glutathione and is then further metabolized to form cysteine and mercapturic acid conjugates.

Acetaminophen metabolites are mainly excreted in the urine. Less than 5% is excreted in the urine as unconjugated (free) acetaminophen and more than 90% of the administered dose is excreted within 24 hours.

13 NONCLINICAL TOXICOLOGY

13.1 Carcinogenesis, Mutagenesis, Impairment of Fertility

Carcinogenesis

Long-term studies in mice and rats have been completed by the National Toxicology Program to evaluate the carcinogenic potential of acetaminophen. In 2-year feeding studies, F344/N rats and B6C3F1 mice were fed a diet containing acetaminophen up to 6,000 ppm. Female rats demonstrated equivocal evidence of carcinogenic activity based on increased incidences of mononuclear cell leukemia at 0.8 times the maximum human daily dose (MHDD) of 4 grams/day, based on a body surface area comparison. In contrast, there was no evidence of carcinogenic activity in male rats (0.7 times) or mice (1.2-1.4 times the MHDD, based on a body surface area comparison).

Mutagenesis

Acetaminophen was not mutagenic in the bacterial reverse mutation assay (Ames test). In contrast, acetaminophen tested positive in the in vitro mouse lymphoma assay and the in vitro chromosomal aberration assay using human lymphocytes. In the published literature, acetaminophen has been reported to be clastogenic when administered a dose of 1,500 mg/kg/day to the rat model (3.6 times the MHDD, based on a body surface area comparison). In contrast, no clastogenicity was noted at a dose of 750 mg/kg/day (1.8 times the MHDD, based on a body surface area comparison), suggesting a threshold effect.

Impairment of Fertility

In studies conducted by the National Toxicology Program, fertility assessments have been completed in Swiss mice via a continuous breeding study. There were no effects on fertility parameters in mice consuming up to 1.7 times the MHDD of acetaminophen, based on a body surface area comparison. Although there was no effect on sperm motility or sperm density in the epididymis, there was a significant increase in the percentage of abnormal sperm in mice consuming 1.7 times the MHDD (based on a body surface area comparison) and there was a reduction in the number of mating pairs producing a fifth litter at this dose, suggesting the potential for cumulative toxicity with chronic administration of acetaminophen near the upper limit of daily dosing.

Published studies in rodents report that oral acetaminophen treatment of male animals at doses that are 1.2 times the MHDD and greater (based on a body surface area comparison) result in decreased testicular weights, reduced spermatogenesis, reduced fertility, and reduced implantation sites in females given the same doses. These effects appear to increase with the duration of treatment.

In a published mouse study, oral administration of 50 mg/kg acetaminophen to pregnant mice from Gestation Day 7 to delivery (0.06 times the MHDD, based on a body surface area comparison) reduced the number of primordial follicles in female offspring and reduced the percentage of full term pregnancies and number of pups born to these females exposed to acetaminophen in utero.

In a published study, oral administration of 350 mg/kg acetaminophen to pregnant rats (0.85 times the MHDD, based on a body surface area comparison) from Gestation Day 13 to 21 (dams) reduced the number of germ cells in the fetal ovary, decreased ovary weight, and reduced the number of pups per litter in F1 females as well as reduced ovary weights in F2 females.

14 CLINICAL STUDIES

14.1 Adult Acute Pain

The efficacy of acetaminophen in the treatment of acute pain in adults was evaluated in two randomized, double-blind, placebo-controlled clinical trials in patients with postoperative pain.

Pain Study 1 evaluated the analgesic efficacy of repeated doses of acetaminophen 1,000 mg vs. placebo every 6 hours for 24 hours in 101 patients with moderate to severe pain following total hip or knee replacement. Acetaminophen was statistically superior to placebo for reduction in pain intensity over 24 hours. There was an attendant decrease in opioid consumption, the clinical benefit of which was not demonstrated.

Pain Study 2 evaluated the analgesic efficacy of repeated doses of acetaminophen 1,000 mg every 6 hours or 650 mg every 4 hours for 24 hours versus placebo in the treatment of 244 patients with moderate to severe postoperative pain after abdominal laparoscopic surgery.

Patients receiving acetaminophen experienced a statistically significant greater reduction in pain intensity over 24 hours compared to placebo.

14.2 Adult Fever

The efficacy of acetaminophen 1,000 mg in the treatment of adult fever was evaluated in one randomized, double-blind, placebo-controlled clinical trial. The study was a 6-hour, single-dose, endotoxin-induced fever study in 60 healthy adult males. A statistically significant antipyretic effect of acetaminophen was demonstrated through 6 hours in comparison to placebo. The mean temperature over time is shown in Figure 1.

Figure 1: Mean Temperature (ºC) Over Time

14.3 Pediatric Acute Pain and Fever

Acetaminophen was studied in 355 pediatric patients in two active-controlled trials and three open-label safety and pharmacokinetic trials [see Use in Specific Populations (8.4)].

16 HOW SUPPLIED/STORAGE AND HANDLING

Acetaminophen Injection is supplied as follows:

Product Code | Unit of Sale | Strength | Unit of Use
434100 | NDC 63323-434-00 Package of 20 Single-dose flexible bags | 1,000 mg per 100 mL (10 mg per mL) | NDC 63323-434-41 100 mL Single-dose flexible bag

Do not remove unit from overwrap until ready for use.

To open, tear outer wrap at the notch and remove solution bag. After removing the outer wrap, check the container for minute leaks by squeezing the solution bag firmly. If leaks are found, discard the solution because the sterility may be impaired. A small amount of moisture may be present inside the outer wrap.

Acetaminophen Injection should be stored at 20°C to 25°C (68° to 77°F); excursions permitted to 15°C to 30°C (59°F to 86°F) [see USP Controlled Room Temperature].

For single use only. The product should be used within 24 hours after opening. Do not refrigerate or freeze.

The container is not made with natural rubber latex. Non-PVC, Non-DEHP, Sterile.

Manufactured for:

Lake Zurich, IL 60047

Made in Norway

www.fresenius-kabi.com/us

451659D

PACKAGE LABEL

PACKAGE LABEL - PRINCIPAL DISPLAY – Acetaminophen 100 mL Bag Label
Acetaminophen NDC 63323-434-41
Injection 434100
1,000 mg per 100 mL
(10 mg per mL)
For Intravenous Infusion Rx Only

PACKAGE LABEL

PACKAGE LABEL - PRINCIPAL DISPLAY - Acetaminophen 100 mL Foil Overwrap
To Open Overwrap - Tear at Notch
Acetaminophen NDC 63323-434-41
Injection 434100
1,000 mg per 100 mL
(10 mg per mL)
For Intravenous Infusion Rx Only

PACKAGE LABEL

PACKAGE LABEL - PRINCIPAL DISPLAY - Acetaminophen 100 mL Case Label

NDC 63323-434-00 434100

Acetaminophen
Injection

1,000 mg per 100 mL
(10 mg per mL)
100 mL x 20